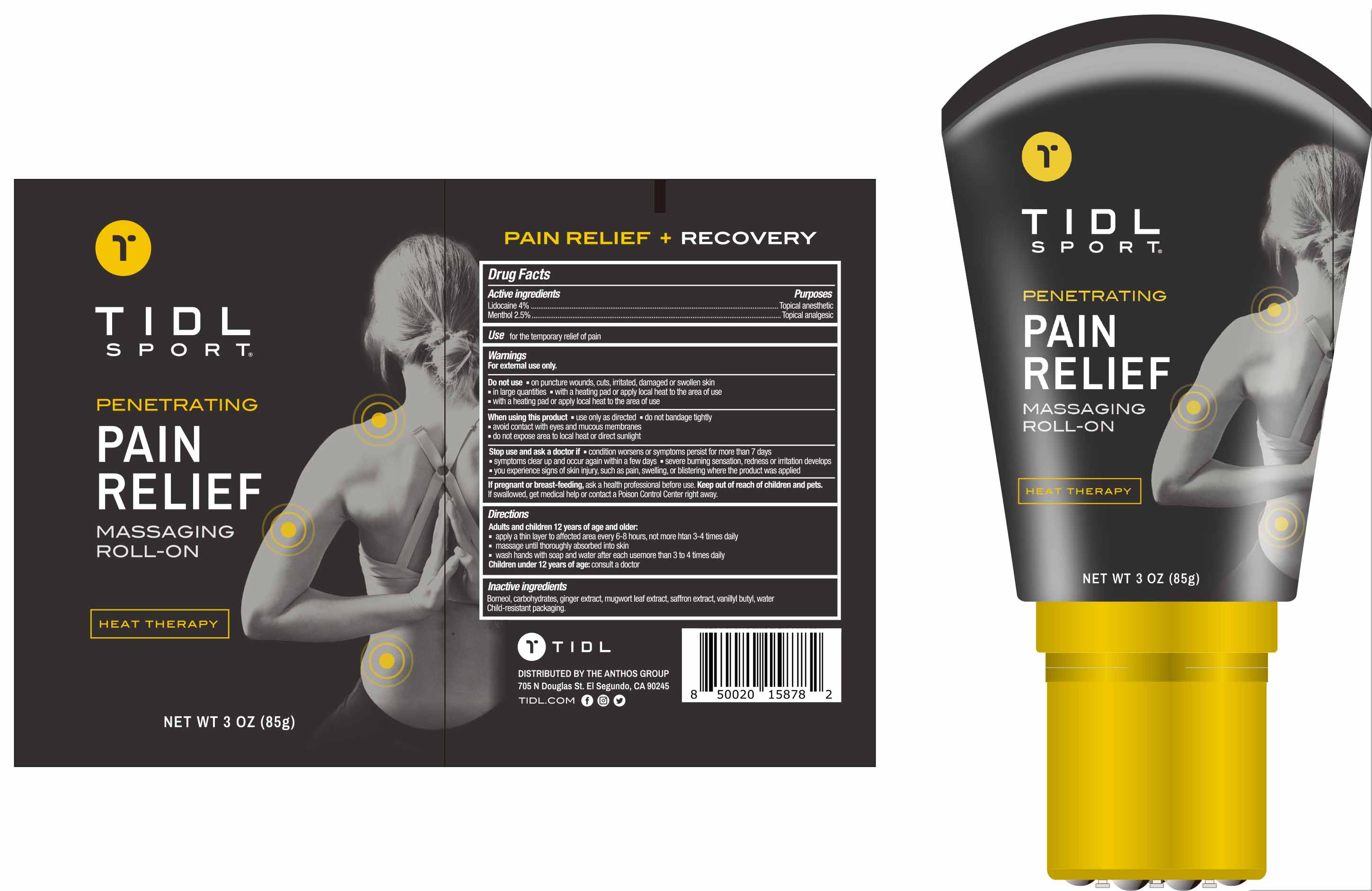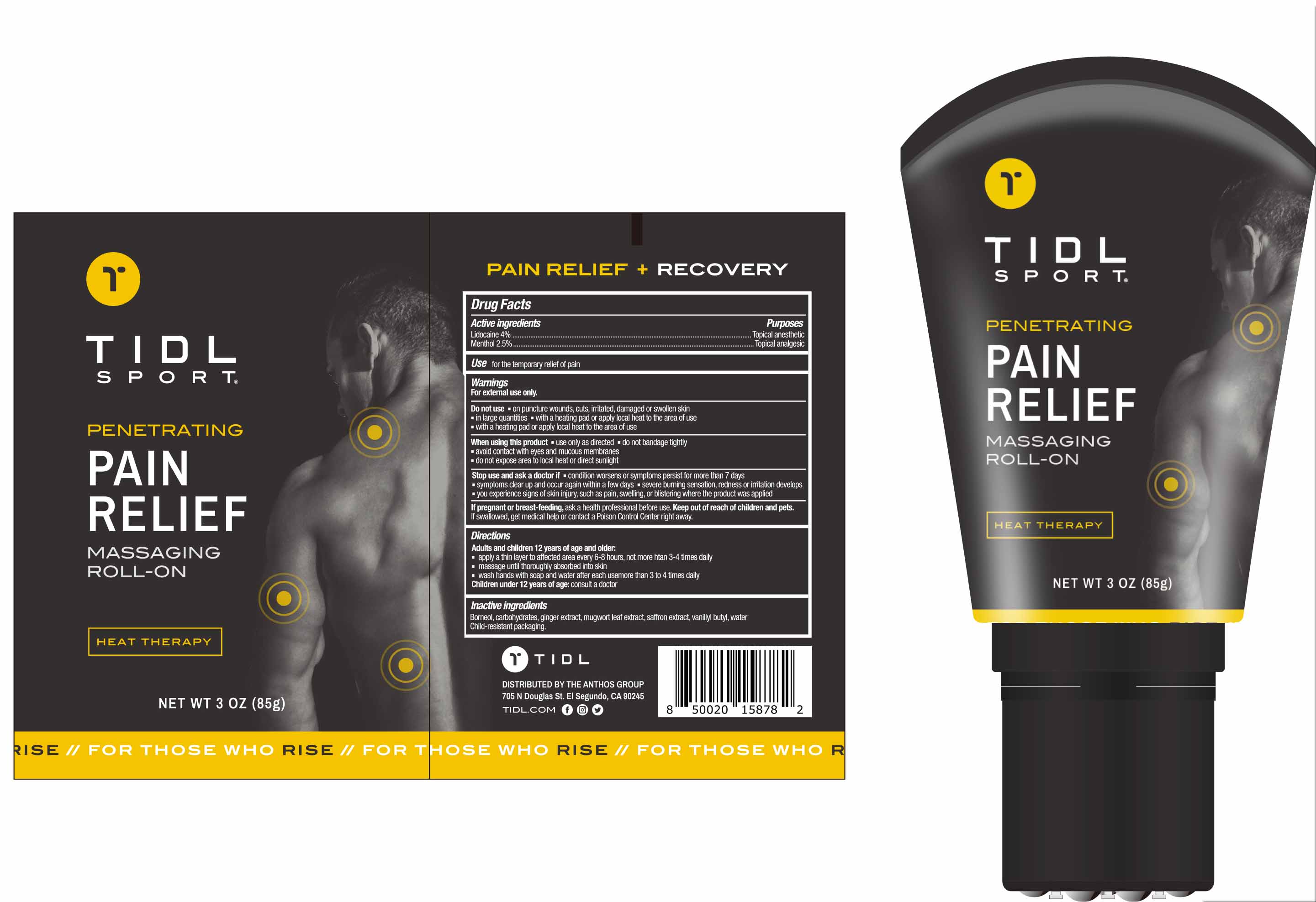 DRUG LABEL: TIDL PAIN RELIEF MASSAGING ROLL-ON
NDC: 79740-011 | Form: LINIMENT
Manufacturer: The Anthos Group
Category: otc | Type: HUMAN OTC DRUG LABEL
Date: 20221026

ACTIVE INGREDIENTS: MENTHOL 2.5 g/100 g; LIDOCAINE 4 g/100 g
INACTIVE INGREDIENTS: SIALYL LEWIS A; GINGER; CROCUS SATIVUS FLOWER; ARTEMISIA PRINCEPS LEAF; ETHYL VANILLIN; WATER; BORNEOL

79740-011
TIDL PAIN RELIEF MASSAGING ROLL-ON

ACTIVE INGREDIENT

Lidocaine 4%,

Menthol 2.5%

PURPOSE

Topical anesthetic

INDICATIONS AND USAGE

Use for the temporary relief of pain

WARNINGS

Wamings
For extemal use only .

KEEP OUT OF REACH OF CHILDREN

If pregnant or breast-feeding , ask a health professional before use . Keep out of reach of children and pets. If swallowed , get medical help or contact a Poison Control Center right away

INACTIVE INGREDIENT

Ginger Extract
Saffron Extract
Water
Mugwort Leaf Extract
Vanillyn Butyl
Borneol
Carbohydrates

Directions

Adults and children 12 years of age and older
apply a thin layer to affected area every 6-8 hours , not more han 3-4 times daily
massage until thoroughly absorbed into skin
wash hands with soap and water after each usemore than 3 to 4 times daily
Children under 12 years of age : consult a doctor

PACKAGE LABEL

79740-011-01

79740-011-02